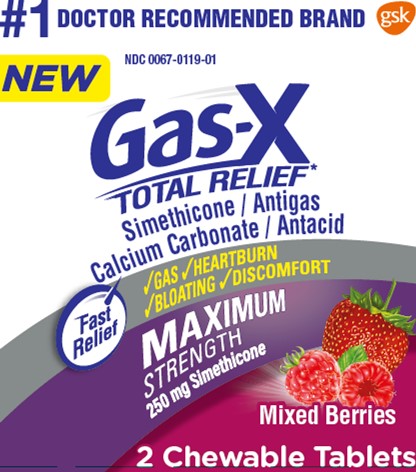 DRUG LABEL: Gas-X

NDC: 0067-0119 | Form: TABLET, CHEWABLE
Manufacturer: Haleon US Holdings LLC
Category: otc | Type: HUMAN OTC DRUG LABEL
Date: 20240405

ACTIVE INGREDIENTS: CALCIUM CARBONATE 750 mg/1 1; DIMETHICONE 250 mg/1 1
INACTIVE INGREDIENTS: ALCOHOL; AMMONIA; YELLOW WAX; CARNAUBA WAX; ANHYDROUS CITRIC ACID; CORN SYRUP; DEXTRIN PALMITATE (CORN; 20000 MW); ETHYL ACETATE; FD&C YELLOW NO. 6; ALUMINUM OXIDE; ACACIA; ISOPROPYL ALCOHOL; MALTODEXTRIN; METHYLPARABEN; BUTYL ALCOHOL; PHOSPHORIC ACID; PROPYLENE GLYCOL; PROPYLPARABEN; WATER; SHELLAC; SORBIC ACID; SORBITOL; LECITHIN, SOYBEAN; SUCROSE; TITANIUM DIOXIDE; CORN OIL

Drug Facts

Active ingredients (per tablet)

Calcium carbonate 750 mg

Simethicone 250 mg

Purpose

Antacid

Antigas

Uses

for the relief of

- pressure, bloating, and fullness commonly referred to as gas
- gas associated with heartburn, sour stomach, or acid indigestion
- acid indigestion
- heartburn
- sour stomach
- upset stomach associated with these symptoms

Warnings

Ask a doctor or pharmacist before use if you are

presently taking a prescription drug. Antacids may interact with certain prescription drugs.

When using this product

- do not exceed 2 tablets in 24 hours except under the advice and supervision of a doctor
- do not use the maximum dosage for more than 2 weeks, except under the advice and supervision of a doctor

Directions

- adults and children 12 years and older:chew 1 or 2 tablets as symptoms occur, or as directed by a doctor. Chew or crush tablets completely before swallowing.
- do not take for symptoms that persist for more than 2 weeks, unless advised by a doctor

Other information

- each tablet contains:elemental calcium 295 mg
- store in a cool, dry place at no higher than 25°C (77°F)

Inactive ingredients

alcohol, ammonium hydroxide, beeswax, carnauba wax, citric acid, corn syrup, dextrin, ethyl acetate, FD&C yellow 6, FD&C yellow 6 lake, flavor, gum arabic, isopropyl alcohol, maltodextrin, methylparaben, n-butyl alcohol, pharmaceutical ink, phosphoric acid, propylene glycol, propylparaben, purified water, shellac, sorbic acid, sorbitol, soy lecithin, sucrose, titanium dioxide, vegetable oil (coconut origin)

Questions or comments?

1-855-328-5204

Additional Information

DO NOT USE IF POUCH IS OPEN OR TORN.

Dist. by: GSK CH,Warren, NJ 07059

Trademarks owned or licensed by GSK.

©2021 GSK or licensor.

Provides gas and heartburn relief

1001388

Principal Display Panel

NEW#1 DOCTOR RECOMMENDED BRAND

NDC 0067-0119-01

Gas-X

TOTAL RELIEF*

Simethicone / Antigas

Calcium Carbonate / Antacid

*Provides gas and heartburn relief

Fast Relief

√ GAS √ HEARTBURN √ BLOATING √ DISCOMFORT

MAXIMUM

STRENGTH

250 mg Simethicone

Mixed Berries

2 Chewable Tablets

1001388 – Front Pouch